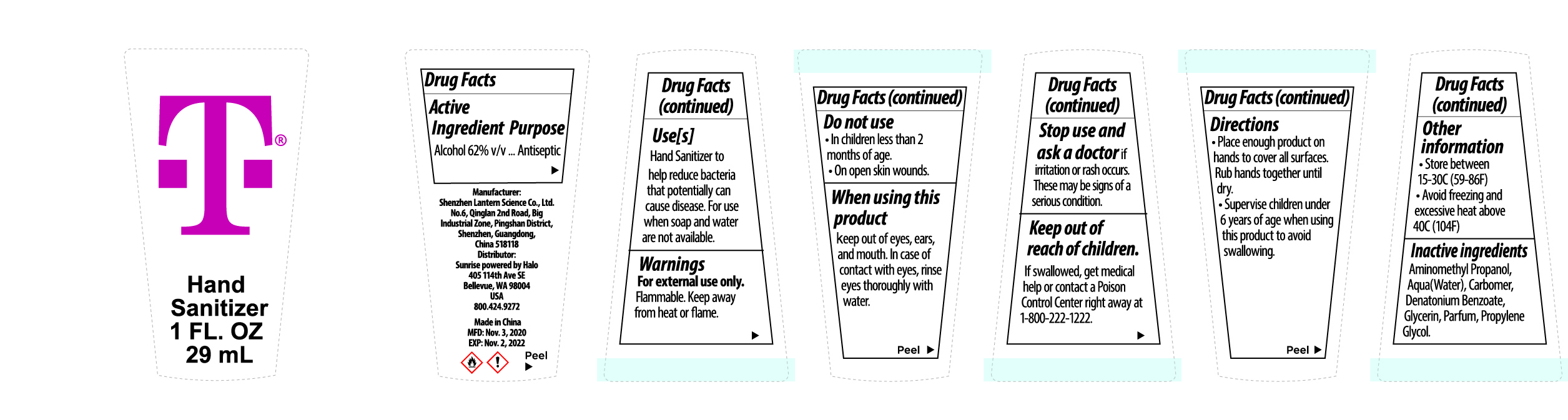 DRUG LABEL: Hand sanitizer 29ml
NDC: 54860-347 | Form: GEL
Manufacturer: Shenzhen Lantern Scicence Co.,Ltd.
Category: otc | Type: HUMAN OTC DRUG LABEL
Date: 20210127

ACTIVE INGREDIENTS: ALCOHOL 62 mL/100 mL
INACTIVE INGREDIENTS: CARBOMER 940 0.28 mL/100 mL; DENATONIUM BENZOATE 0.0005 mL/100 mL; AMINOMETHYLPROPANOL 0.1 mL/100 mL; LEMON 0.1 mL/100 mL; PROPYLENE GLYCOL 0.1 mL/100 mL; WATER 37.3195 mL/100 mL; GLYCERIN 0.1 mL/100 mL

Hand sanitizer 29ml

Active Ingredient

Active Ingredient Purpose

Ethyl Alcohol 62%（V/V） Antiseptic

keep out of reach of children

If swallowed,get medical help or contact a Poison Control Center right away at 1-800-222-1222

DOSAGE AND ADMINISTRATION

Recommended for repeated use.

use anywhere without water.

Warning

For external use only,Flammable,Keep away from heat or flame.

WARNINGS AND PRECAUTIONS

For external use only.

Flammable, keep away from heat and flame.

STOP USE

Discontinue if skin becomes irritated and ask a doctor .

Keep out of reach of children. In case of accidental ingestion, seek professional assistance or contact a poson control center immediately.

Inactive ingredients

Aminomethyl propanol,Water,Carbomer,Deatonium Benzoate,Glycerin,Parfum,Propylene glycol.

Directions

place enough product on hands to cover all surfaces,Rub hands together until dry.Supervise children under 6 years of age when using this product to avoid swallowing.

When using this product

keep out of eyes. In case of contact with eyes, flush thoroughly with water.

Do not inhale or ingest.

Avoid contact with broken skin.

Other information

Do not store above 105F.

May discolor some fabrics.

Harmful to wood finishes and plastics.

When using this product

Keep out of eyes,ears,and mouth.In case of contact with eyes.rinse eyes thoroughly with water.

Purpose

Antiseptic

Stop use and ask a doctor

if irritation or rash occurs,these may be signs of a serious condition.

Use

Hand sanitizer to help reduce bacteria that petentially can cause disease.For use when soap and water are not available.

Other information

Store between 15-30C(59-86F).Avoid freezing or excessive heat above 40C(104F).

Do not use

in children less than 2 months of age

on open skin wounds.